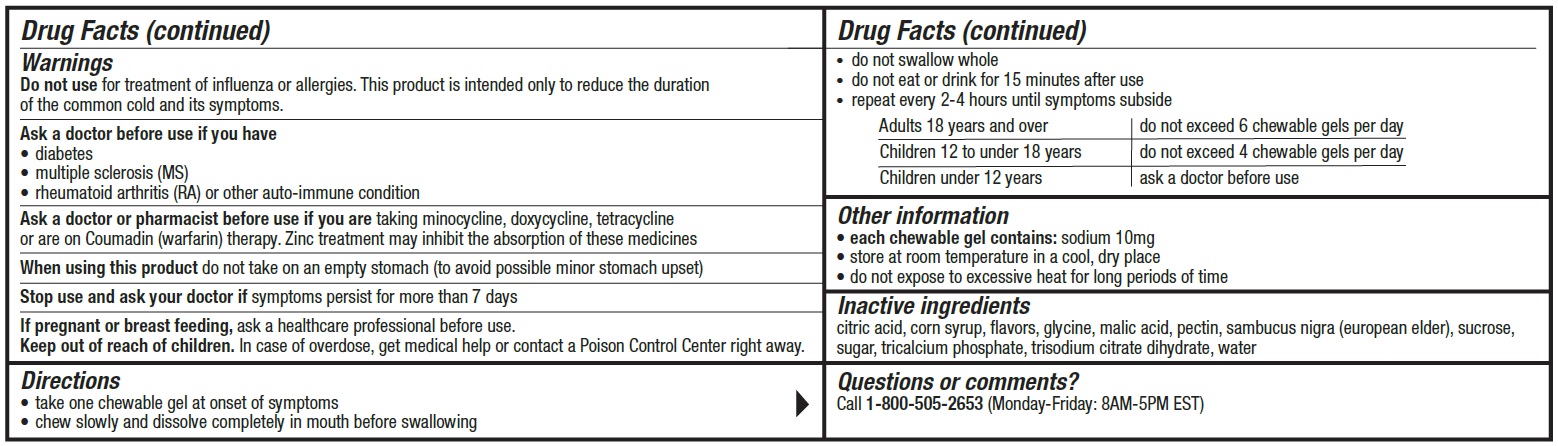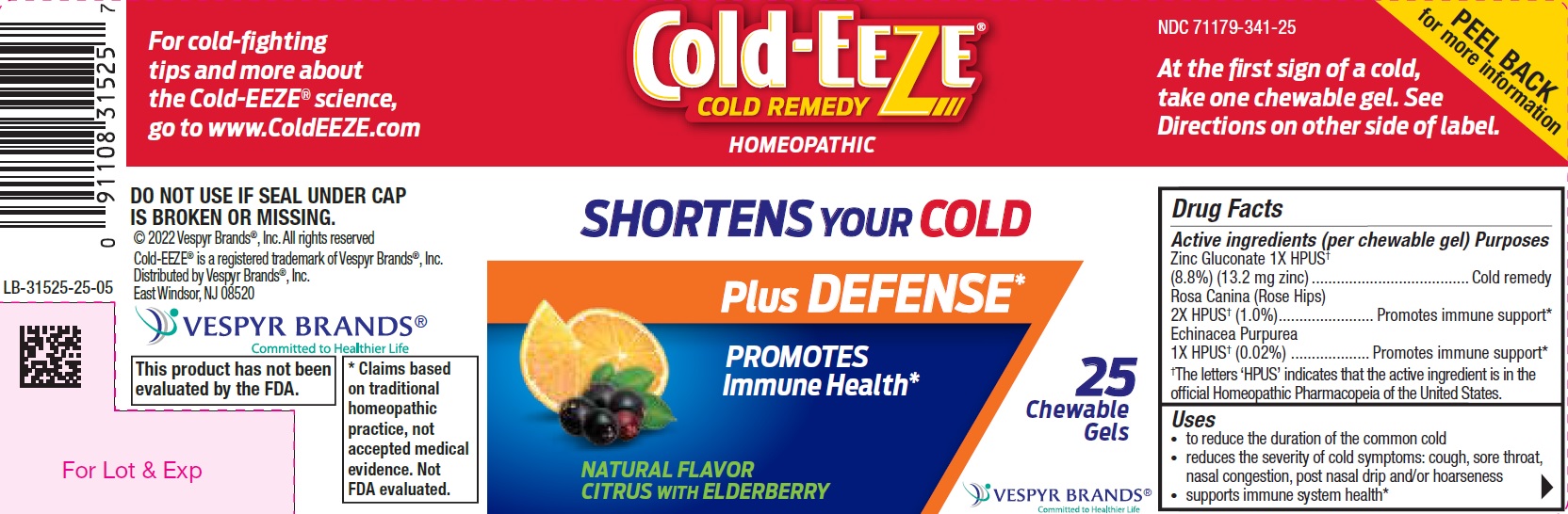 DRUG LABEL: Cold-EEZE Cold Remedy
NDC: 71179-341 | Form: CHEWABLE GEL
Manufacturer: Vespyr Brands Inc
Category: homeopathic | Type: HUMAN OTC DRUG LABEL
Date: 20230914

ACTIVE INGREDIENTS: ROSA CANINA FRUIT 2 mg/1 1; ECHINACEA PURPUREA 1 mg/1 1; ZINC GLUCONATE 13.2 mg/1 1
INACTIVE INGREDIENTS: SUGARCANE; SAMBUCUS NIGRA FLOWER; TRISODIUM CITRATE DIHYDRATE; GLYCINE; SUCROSE; CORN SYRUP; MALIC ACID; TRICALCIUM PHOSPHATE; WATER; PECTIN; CITRIC ACID MONOHYDRATE

Cold-EEZE Cold Remedy Chewable gels/gummies

Active ingredients

Active ingredients (per lozenge) . . . . . . . . . . . . . . . . . . . . . . Purposes
Zinc Gluconate 1X HPUS† (8.8%) (13.2 mg zinc).................... Cold Remedy
Rosa Caina (Rose Hips) 2X HPUS† (1.0%) ............................ Promotes immune support*
Echinacea Purpurea 1X HPUS† (0.02%)................................... Promotes immune support*
† The letters ‘HPUS’ indicate that the active ingredient is in the official Homeopathic Pharmacopeia of the United States.

Purposes

Uses

- to reduce the duration of the common cold
- reduces the severity of cold symptoms: cough, sore throat, nasal congestion, post nasal drip and/or hoarseness
- supports immune system health*

Warnings

Do not use for treatment of influenza or allergies. This product is intended only to reduce the duration of the common cold and provide relief of cold and flu symptoms.

Ask a doctor before use if you have
• diabetes

• multiple sclerosis (MS)

• rheumatoid arthritis (RA) or other auto-immune condition

Ask a doctor or pharmacist before use if you are taking minocycline, doxycycline, tetracycline or are on Coumadin (warfarin) therapy. Zinc treatment may inhibit the absorption of these medicines.

When using this product do not take on an empty stomach (to avoid possible minor stomach upset)

Stop use and ask your doctor if symptoms persist more than 7 days

PREGNANCY OR BREAST FEEDING

If pregnant or breastfeeding, ask a healthcare professional before use.

Keep out of reach of children. In case of overdose, get medical help or contact a Poison Control Center right away.

Directions

• take one chewable gel at onset of symptoms

• chew slowly and dissolve completely in mouth before swallowing
• do not swallow whole
• do not eat or drink for 15 minutes after use
• repeat every 2-4 hours until symptoms subside

Adults 18 years and over | do not exceed 6 chewable gels per day
Children 12 to under 18 years | do not exceed 4 chewable gels per day
Children under 12 years | ask a doctor before use

Other information

- each chewable gel contains: sodium 10 mg

- store at room temperature in a cool, dry place
- do not expose to excessive heat for long periods of time

Inactive ingredients

citric acid, corn syrup, flavors, glycine, malic acid, pectin, sambucus nigra (european elder), sucrose, sugar, tricalcium phosphate, trisodium citrate dihydrate, water

Questions?

call 1-800-505-2653 (Mon – Fri: 8AM – 5PM EST)

PACKAGE LABEL

Cold-EEZE®

COLD REMEDY

HOMEOPATHIC

SHORTENS YOUR COLD

Plus DEFENSE*

PROMOTES Immune Health*

NATURAL FLAVOR CITRUS WITH ELDERBERRY

25 Chewable Gels

©2022 Vespyr Brands®, Inc.

Cold-EEZE® is a registred trademark of Vespyr Brands®, Inc.

Distributed by Vespyr Brands®, Inc.

East Windsor, NJ 08520

This product has not been evaluated by the FDA

*Claims based on traditional homeopathic practice, not accepted medical evidence. Not FDA evaluated.